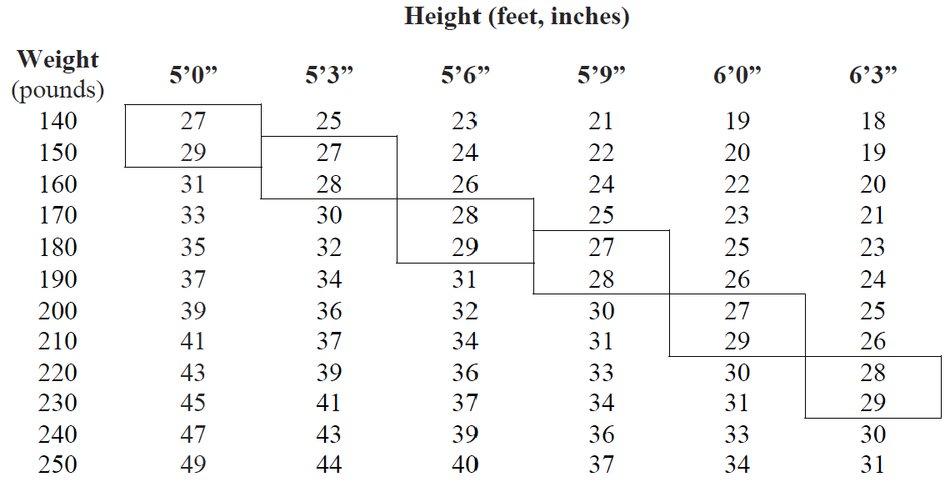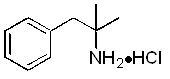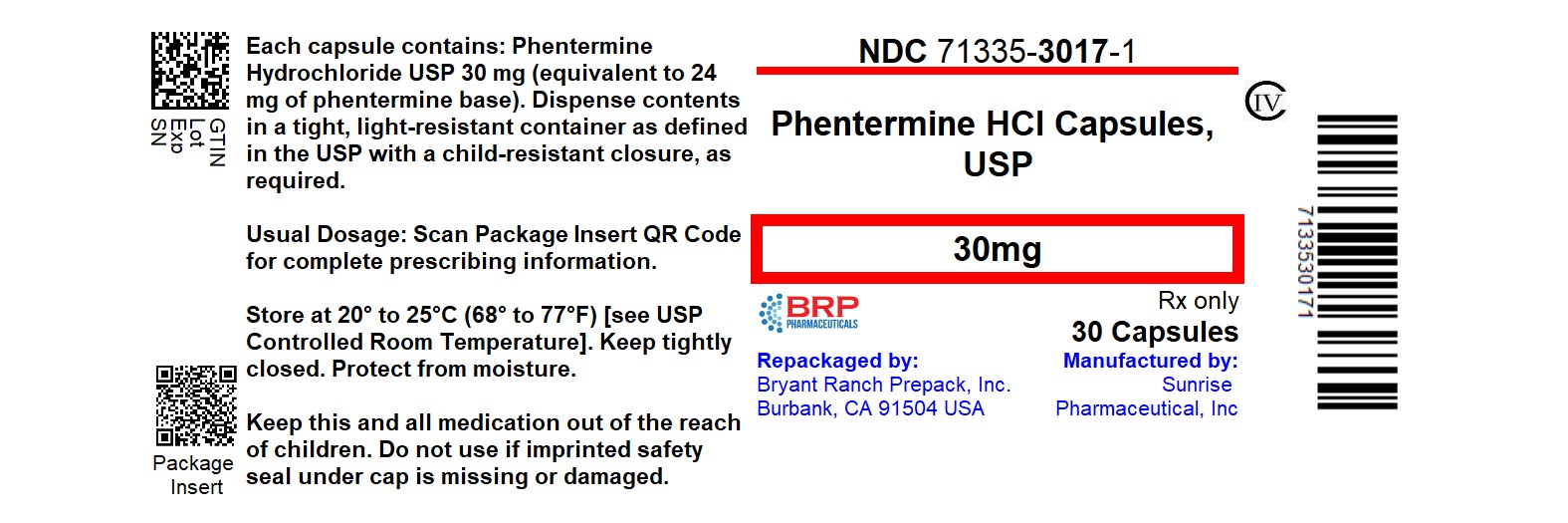 DRUG LABEL: Phentermine Hydrochloride
NDC: 71335-3017 | Form: CAPSULE
Manufacturer: Bryant Ranch Prepack
Category: prescription | Type: HUMAN PRESCRIPTION DRUG LABEL
Date: 20260204
DEA Schedule: CIV

ACTIVE INGREDIENTS: PHENTERMINE HYDROCHLORIDE 30 mg/1 1
INACTIVE INGREDIENTS: SILICON DIOXIDE; STARCH, CORN; GELATIN, UNSPECIFIED; LACTOSE MONOHYDRATE; MAGNESIUM STEARATE; D&C RED NO. 28; FD&C BLUE NO. 1; SHELLAC; ALCOHOL; ISOPROPYL ALCOHOL; BUTYL ALCOHOL; PROPYLENE GLYCOL; WATER; AMMONIA; POTASSIUM HYDROXIDE; FERROSOFERRIC OXIDE

HIGHLIGHTS OF PRESCRIBING INFORMATION

These highlights do not include all the information needed to use Phentermine Hydrochloride Capsules USP safely and effectively. See full prescribing information for Phentermine Hydrochloride Capsules USP.
PHENTERMINE hydrochloride capsules USP, for oral use CIV
Initial U.S. Approval: 1959

1 INDICATIONS AND USAGE

Phentermine hydrochloride is a sympathomimetic amine anorectic indicated as a short-term adjunct (a few weeks) in a regimen of weight reduction based on exercise, behavioral modification and caloric restriction in the management of exogenous obesity for patients with an initial body mass index ≥ 30 kg/m^2, or ≥ 27 kg/m^2 in the presence of other risk factors (e.g., controlled hypertension, diabetes, hyperlipidemia).

The limited usefulness of agents of this class, including phentermine hydrochloride, should be measured against possible risk factors inherent in their use.

2 DOSAGE AND ADMINISTRATION

- Dosage should be individualized to obtain an adequate response with the lowest effective dose. (2.1)
- Late evening administration should be avoided (risk of insomnia). (2.1)
- Phentermine hydrochloride capsules can be taken with or without food (2.1)
- Limit the dosage to 15 mg daily for patients with severe renal impairment (eGFR 15 to 29 mL/min/1.73m^2)- (2.2)

3 DOSAGE FORMS AND STRENGTHS

- Capsules containing 15 mg or 30 mg phentermine hydrochloride. (3)

4 CONTRAINDICATIONS

- History of cardiovascular disease (e.g., coronary artery disease, stroke, arrhythmias, congestive heart failure, uncontrolled hypertension) (4)
- During or within 14 days following the administration of monoamine oxidase inhibitors (4)
- Hyperthyroidism (4)
- Glaucoma (4)
- Agitated states (4)
- History of drug abuse (4)
- Pregnancy (4, 8.1)
- Nursing (4, 8.3)
- Known hypersensitivity, or idiosyncrasy to the sympathomimetic amines (4)

5 WARNINGS AND PRECAUTIONS

- Co-administration with other drugs for weight loss is not recommended (safety and efficacy of combination not established). (5.1)
- Rare cases of primary pulmonary hypertension have been reported. Phentermine should be discontinued in case of new, unexplained symptoms of dyspnea, angina pectoris, syncope or lower extremity edema. (5.2)
- Rare cases of serious regurgitant cardiac valvular disease have been reported. (5.3)
- Tolerance to the anorectic effect usually develops within a few weeks. If this occurs, phentermine should be discontinued. The recommended dose should not be exceeded. (5.4)
- Phentermine may impair the ability of the patient to engage in potentially hazardous activities such as operating machinery or driving a motor vehicle. (5.5)
- Risk of abuse and dependence. The least amount feasible should be prescribed or dispensed at one time in order to minimize the possibility of overdosage. (5.6)
- Concomitant alcohol use may result in an adverse drug reaction. (5.7)
- Use caution in patients with even mild hypertension (risk of increase in blood pressure). (5.8)
- A reduction in dose of insulin or oral hypoglycemic medication may be required in some patients. (5.9)

6 ADVERSE REACTIONS

Adverse events have been reported in the cardiovascular, central nervous, gastrointestinal, allergic, and endocrine systems.

To report SUSPECTED ADVERSE REACTIONS, contact Sunrise Pharmaceutical, Inc. at 732-382-6085 or FDA at 1-800-FDA-1088 or www.fda.gov/medwatch.

7 DRUG INTERACTIONS

- Monoamine oxidase inhibitors: Risk of hypertensive crisis. (4, 7.1)
- Alcohol: Consider potential interaction (7.2)
- Insulin and oral hypoglycemics: Requirements may be altered. (7.3)
- Adrenergic neuron blocking drugs: Hypotensive effect may be decreased by phentermine. (7.4)

8 USE IN SPECIFIC POPULATIONS

- Nursing mothers: Discontinue drug or nursing taking into consideration importance of drug to mother. (4, 8.3)
- Pediatric use: Safety and effectiveness not established. (8.4)
- Geriatric use: Due to substantial renal excretion, use with caution. (8.5)
- Renal Impairment: Avoid use in patients with eGFR less than 15 mL/min/m^2 or end-stage renal disease requiring dialysis. (8.6)

FULL PRESCRIBING INFORMATION

1 INDICATIONS AND USAGE

Phentermine hydrochloride capsules are indicated as a short-term (a few weeks) adjunct in a regimen of weight reduction based on exercise, behavioral modification and caloric restriction in the management of exogenous obesity for patients with an initial body mass index ≥ 30 kg/m^2, or ≥ 27 kg/m^2 in the presence of other risk factors (e.g., controlled hypertension, diabetes, hyperlipidemia).

Below is a chart of body mass index (BMI) based on various heights and weights.

BMI is calculated by taking the patient’s weight, in kilograms (kg), divided by the patient’s height, in meters (m), squared. Metric conversions are as follows: pounds ÷ 2.2 = kg; inches x 0.0254 = meters.

BODY MASS INDEX (BMI), kg/m^2

The limited usefulness of agents of this class, including phentermine, [see CLINICAL PHARMACOLOGY (12.1, 12.2)] should be measured against possible risk factors inherent in their use such as those described below.

2 DOSAGE AND ADMINISTRATION

2.1 Exogenous Obesity

Dosage should be individualized to obtain an adequate response with the lowest effective dose.
The usual adult dose is 15 mg to 30 mg as prescribed by the physician, at approximately 2 hours after breakfast for appetite control. Administration of one 30 mg capsule daily has been found to be adequate in depression of the appetite for 12 to 14 hours. Phentermine is not recommended for use in pediatric patients ≤16 years of age.
Late evening medication should be avoided because of the possibility of resulting insomnia.

2.2 Dosage in Patients With Renal Impairment

The recommended maximum dosage of phentermine hydrochloride is 15 mg daily for patients with severe renal impairment (eGFR 15 to 29 mL/min/1.73m^2). Avoid use of phentermine hydrochloride in patients with eGFR less than 15 mL/min/1.73m^2 or end-stage renal disease requiring dialysis [see USE IN SPECIFIC POPULATIONS (8.6) and CLINICAL PHARMACOLOGY (12.3)].

3 DOSAGE FORMS AND STRENGTHS

Capsules containing 15 mg or 30 mg phentermine hydrochloride (equivalent to 12 mg or 24 mg phentermine base, respectively).

15 mg capsules: gray opaque cap, yellow opaque body with black imprint “N1” on both the cap and body, filled with powder.

30 mg capsules: blue cap, natural body with black imprint “N16” on both the cap and body, filled with powder.

4 CONTRAINDICATIONS

• History of cardiovascular disease (e.g., coronary artery disease, stroke, arrhythmias, congestive heart failure, uncontrolled hypertension)
• During or within 14 days following the administration of monoamine oxidase inhibitors
• Hyperthyroidism
• Glaucoma
• Agitated states
• History of drug abuse
• Pregnancy [see USE IN SPECIFIC POPULATIONS (8.1)]
• Nursing [see USE IN SPECIFIC POPULATIONS (8.3)]
• Known hypersensitivity, or idiosyncrasy to the sympathomimetic amines

5 WARNINGS AND PRECAUTIONS

5.1 Co-administration with Other Drug Products for Weight Loss

Phentermine hydrochloride capsules are indicated only as short-term (a few weeks) monotherapy for the management of exogenous obesity. The safety and efficacy of combination therapy with phentermine and any other drug products for weight loss including prescribed drugs, over-the-counter preparations, and herbal products, or serotonergic agents such as selective serotonin reuptake inhibitors (e.g., fluoxetine, sertraline, fluvoxamine, paroxetine), have not been established. Therefore, co-administration of phentermine and these drug products is not recommended.

5.2 Primary Pulmonary Hypertension

Primary Pulmonary Hypertension (PPH) – a rare, frequently fatal disease of the lungs – has been reported to occur in patients receiving a combination of phentermine with fenfluramine or dexfenfluramine. The possibility of an association between PPH and the use of phentermine alone cannot be ruled out; there have been rare cases of PPH in patients who reportedly have taken phentermine alone. The initial symptom of PPH is usually dyspnea. Other initial symptoms may include angina pectoris, syncope or lower extremity edema. Patients should be advised to report immediately any deterioration in exercise tolerance. Treatment should be discontinued in patients who develop new, unexplained symptoms of dyspnea, angina pectoris, syncope or lower extremity edema, and patients should be evaluated for the possible presence of pulmonary hypertension.

5.3 Valvular Heart Disease

Serious regurgitant cardiac valvular disease, primarily affecting the mitral, aortic and/or tricuspid valves, has been reported in otherwise healthy persons who had taken a combination of phentermine with fenfluramine or dexfenfluramine for weight loss. The possible role of phentermine in the etiology of these valvulopathies has not been established and their course in individuals after the drugs are stopped is not known. The possibility of an association between valvular heart disease and the use of phentermine alone cannot be ruled out; there have been rare cases of valvular heart disease in patients who reportedly have taken phentermine alone.

5.4 Development of Tolerance, Discontinuation in Case of Tolerance

When tolerance to the anorectant effect develops, the recommended dose should not be exceeded in an attempt to increase the effect; rather, the drug should be discontinued.

5.5 Effect on the Ability to Engage in Potentially Hazardous Tasks

Phentermine may impair the ability of the patient to engage in potentially hazardous activities such as operating machinery or driving a motor vehicle; the patient should therefore be cautioned accordingly.

5.6 Risk of Abuse and Dependence

Phentermine is related chemically and pharmacologically to amphetamine (d- and dllamphetamine) and other related stimulant drugs have been extensively abused. The possibility of abuse of phentermine should be kept in mind when evaluating the desirability of including a drug as part of a weight reduction program. See DRUG ABUSE AND DEPENDENCE (9) and OVERDOSAGE (10).

The least amount feasible should be prescribed or dispensed at one time in order to minimize the possibility of overdosage.

5.7 Usage with Alcohol

Concomitant use of alcohol with phentermine may result in an adverse drug reaction.

5.8 Use in Patients with Hypertension

Use caution in prescribing phentermine for patients with even mild hypertension (risk of increase in blood pressure).

5.9 Use in Patients on Insulin or Oral Hypoglycemic Medications for Diabetes Mellitus

A reduction in insulin or oral hypoglycemic medications in patients with diabetes mellitus may be required.

5.10 Risk of Allergic Reactions due to Tartrazine

Phentermine hydrochloride capsule, 15 mg contains FD&C Yellow No. 5 (tartrazine) which may cause allergic-type reactions (including bronchial asthma) in certain susceptible persons. Although the overall incidence of FD&C Yellow No. 5 (tartrazine) sensitivity in the general populations is low, it is frequently seen in patients who also have aspirin hypersensitivity.

6 ADVERSE REACTIONS

The following adverse reactions are described, or described in greater detail, in other sections:

• Primary pulmonary hypertension [see WARNINGS AND PRECAUTIONS (5.2)]

• Valvular heart disease [see WARNINGS AND PRECAUTIONS (5.3)]

• Effect on the ability to engage in potentially hazardous tasks [see WARNINGS AND PRECAUTIONS (5.5)]

• Withdrawal effects following prolonged high dosage administration [see DRUG ABUSE AND DEPENDENCE (9.3)]. The following adverse reactions to phentermine have been identified:

Cardiovascular
Primary pulmonary hypertension and/or regurgitant cardiac valvular disease, palpitation, tachycardia, elevation of blood pressure, ischemic events.

Central Nervous System
Overstimulation, restlessness, dizziness, insomnia, euphoria, dysphoria, tremor, headache, psychosis.

Gastrointestinal
Dryness of the mouth, unpleasant taste, diarrhea, constipation, other gastrointestinal disturbances.

Allergic
Urticaria.

Endocrine
Impotence, changes in libido.

7 DRUG INTERACTIONS

7.1 Monoamine Oxidase Inhibitors

Use of phentermine is contraindicated during or within 14 days following the administration of monoamine oxidase inhibitors because of the risk of hypertensive crisis.

7.2 Alcohol

Concomitant use of alcohol with phentermine may result in an adverse drug reaction.

7.3 Insulin and Oral Hypoglycemic Medications

Requirements may be altered [see WARNINGS AND PRECAUTIONS (5.9)].

7.4 Adrenergic Neuron Blocking Drugs

Phentermine may decrease the hypotensive effect of adrenergic neuron blocking drugs.

8 USE IN SPECIFIC POPULATIONS

8.1 Pregnancy

Pregnancy category X
Phentermine is contraindicated during pregnancy because weight loss offers no potential benefit to a pregnant woman and may result in fetal harm. A minimum weight gain, and no weight loss, is currently recommended for all pregnant women, including those who are already overweight or obese, due to obligatory weight gain that occurs in maternal tissues during pregnancy. Phentermine has pharmacologic activity similar to amphetamine (d- and dll-amphetamine) [see CLINICAL PHARMACOLOGY (12.1)]. Animal reproduction studies have not been conducted with phentermine. If this drug is used during pregnancy, or if the patient becomes pregnant while taking this drug, the patient should be apprised of the potential hazard to a fetus.

8.3 Nursing Mothers

It is not known if phentermine is excreted in human milk; however, other amphetamines are present in human milk. Because of the potential for serious adverse reactions in nursing infants, a decision should be made whether to discontinue nursing or to discontinue the drug, taking into account the importance of the drug to the mother.

8.4 Pediatric Use

Safety and effectiveness in pediatric patients have not been established. Because pediatric obesity is a chronic condition requiring long-term treatment, the use of this product, approved for short-term therapy, is not recommended.

8.5 Geriatric Use

In general, dose selection for an elderly patient should be cautious, usually starting at the low end of the dosing range, reflecting the greater frequency of decreased hepatic, renal, or cardiac function, and of concomitant disease or other drug therapy.

This drug is known to be substantially excreted by the kidney, and the risk of toxic reactions to this drug may be greater in patients with impaired renal function. Because elderly patients are more likely to have decreased renal function, care should be taken in dose selection, and it may be useful to monitor renal function.

8.6 Renal Impairment

Based on the reported excretion of phentermine in urine, exposure increases can be expected in patients with renal impairment [see CLINICAL PHARMACOLOGY (12.3)].
Use caution when administering phentermine to patients with renal impairment. In patients with severe renal impairment (eGFR 15 to 29 mL/min/1.73m^2), limit the dosage of phentermine to 15 mg daily [see DOSAGE AND ADMINISTRATION (2.2)]. Phentermine has not been studied in patients with eGFR less than 15 mL/min/m^2, including end-stage renal disease requiring dialysis; avoid use in these populations.

9 DRUG ABUSE AND DEPENDENCE

9.1 Controlled Substance

Phentermine is a Schedule IV controlled substance.

9.2 Abuse

Phentermine is related chemically and pharmacologically to the amphetamines. Amphetamines and other stimulant drugs have been extensively abused and the possibility of abuse of phentermine should be kept in mind when evaluating the desirability of including a drug as part of a weight reduction program.

9.3 Dependence

Abuse of amphetamines and related drugs may be associated with intense psychological dependence and severe social dysfunction. There are reports of patients who have increased the dosage of these drugs to many times than recommended. Abrupt cessation following prolonged high dosage administration results in extreme fatigue and mental depression; changes are also noted on the sleep EEG. Manifestations of chronic intoxication with anorectic drugs include severe dermatoses, marked insomnia, irritability, hyperactivity and personality changes. A severe manifestation of chronic intoxication is psychosis, often clinically indistinguishable from schizophrenia.

10 OVERDOSAGE

The least amount feasible should be prescribed or dispensed at one time in order to minimize the possibility of overdosage.

10.1 Acute Overdosage

Manifestations of acute overdosage include restlessness, tremor, hyperreflexia, rapid respiration, confusion, assaultiveness, hallucinations, and panic states. Fatigue and depression usually follow the central stimulation. Cardiovascular effects include arrhythmia, hypertension or hypotension, and circulatory collapse. Gastrointestinal symptoms include nausea, vomiting, diarrhea and abdominal cramps. Overdosage of pharmacologically similar compounds has resulted in fatal poisoning usually terminates in convulsions and coma.

Management of acute phentermine hydrochloride intoxication is largely symptomatic and includes lavage and sedation with a barbiturate. Experience with hemodialysis or peritoneal dialysis is inadequate to permit recommendations in this regard. Acidification of the urine increases phentermine excretion. Intravenous phentolamine (Regitine®, CIBA) has been suggested on pharmacologic grounds for possible acute, severe hypertension, if this complicates overdosage.

10.2 Chronic Intoxication

Manifestations of chronic intoxication with anorectic drugs include severe dermatoses, marked insomnia, irritability, hyperactivity and personality changes. The most severe manifestation of chronic intoxications is psychosis, often clinically indistinguishable from schizophrenia. See DRUG ABUSE AND DEPENDENCE (9.3).

11 DESCRIPTION

Phentermine hydrochloride is a sympathomimetic amine anorectic. Its chemical name is α,α, dimethylphenethylamine hydrochloride. The structural formula is as follows:

C10H15N•HCl M.W. 185.7

Phentermine hydrochloride is a white, odorless, hygroscopic, crystalline powder which is soluble in water and lower alcohols, slightly soluble in chloroform and insoluble in ether.

Phentermine hydrochloride capsule USP is available as an oral capsule containing 15 mg or 30 mg of phentermine hydrochloride (equivalent to 12 mg or 24 mg of phentermine base).

a) powder-filled capsules containing 15 mg phentermine hydrochloride (equivalent to 12 mg phentermine) or 30 mg phentermine hydrochloride (equivalent to 24 mg phentermine) and inactive ingredients: colloidal silicon dioxide, corn starch, gelatin, lactose monohydrate, magnesium stearate.

In addition, the 15 mg capsules contain black iron oxide, FD&C red No. 3, FD&C yellow No. 5, titanium dioxide; and the blue and clear 30 mg capsules contain D&C red No. 28, FD&C blue No. 1. The ingredients in the black imprinting ink are shellac, dehydrated alcohol, isopropyl alcohol, butyl alcohol, propylene glycol, purified water, strong ammonia solution, potassium hydroxide and black iron oxide.

12 CLINICAL PHARMACOLOGY

12.1 Mechanism of Action

Phentermine is a sympathomimetic amine with pharmacologic activity similar to the prototype drugs of this class used in obesity, amphetamine (d- and dll-amphetamine). Drugs of this class used in obesity are commonly known as “anorectics” or “anorexigenics.” It has not been established that the primary action of such drugs in treating obesity is one of appetite suppression since other central nervous system actions, or metabolic effects, may also be involved.

12.2 Pharmacodynamics

Typical of amphetamines include central nervous system stimulation and elevation of blood pressure. Tachyphylaxis and tolerance have been demonstrated with all drugs of this class in which these phenomena have been looked for.

12.3 Pharmacokinetics

Following the administration of phentermine, phentermine reaches peak concentrations (Cmax) after 3 to 4.4 hours.
Specific Populations

Renal Impairment

Cumulative urinary excretion of phentermine under uncontrolled urinary pH conditions was 62% - 85%.
Systemic exposure of phentermine may increase up to 91%, 45%, and 22% in patients with severe, moderate, and mild renal impairment, respectively [see DOSAGE AND ADMINISTRATION (2.2) and USE IN SPECIFIC POPULATIONS (8.6)].

Drug Interactions

In a single-dose study comparing the exposures after oral administration of a combination capsule of 15 mg phentermine and 92 mg topiramate to the exposures after oral administration of a 15 mg phentermine capsule or a 92 mg topiramate capsule, there is no significant topiramate exposure change in the presence of phentermine. However in the presence of topiramate, phentermine Cmax and AUC increase 13% and 42%, respectively.

13 NONCLINICAL TOXICOLOGY

13.1 Carcinogenesis, Mutagenesis, Impairment of Fertility

Studies have not been performed with phentermine to determine the potential for carcinogenesis, mutagenesis or impairment of fertility.

14 CLINICAL STUDIES

In relatively short-term clinical trials, adult obese subjects instructed in dietary management and treated with “anorectic” drugs lost more weight on the average than those treated with placebo and diet.

The magnitude of increased weight loss of drug-treated patients over placebo-treated patients is only a fraction of a pound a week. The rate of weight loss is greatest in the first weeks of therapy for both drug and placebo subjects and tends to decrease in succeeding weeks. The possible origins of the increased weight loss due to the various drug effects are not established. The amount of weight loss associated with the use of an “anorectic” drug varies from trial to trial, and the increased weight loss appears to be related in part to variables other than the drugs prescribed, such as the physician-investigator, the population treated and the diet prescribed. Studies do not permit conclusions as to the relative importance of the drug and non-drug factors on weight loss.

The natural history of obesity is measured over several years, whereas the studies cited are restricted to a few weeks’ duration; thus, the total impact of drug-induced weight loss over that of diet alone must be considered clinically limited.

16 HOW SUPPLIED/STORAGE AND HANDLING

Phentermine hydrochloride capsules USP, for oral administration, are available as:

30 mg: Blue/Clear powder filled capsules; imprinted “N16” in black ink and supplied as:

- NDC 71335-3017-1: 30 Capsules in a BOTTLE
- NDC 71335-3017-2: 42 Capsules in a BOTTLE
- NDC 71335-3017-3: 14 Capsules in a BOTTLE
- NDC 71335-3017-4: 20 Capsules in a BOTTLE
- NDC 71335-3017-5: 28 Capsules in a BOTTLE
- NDC 71335-3017-6: 60 Capsules in a BOTTLE

Store at 20° to 25°C (68° to 77°F) [see USP Controlled Room Temperature].

Protect from moisture.

Dispense in a tight, light-resistant container as defined in the USP, with a child-resistant closure (as required).

Keep out of the reach of children.

Repackaged/Relabeled by:
Bryant Ranch Prepack
Burbank, CA 91504

17 PATIENT COUNSELING INFORMATION

Patients must be informed that phentermine hydrochloride is a short-term (a few weeks) adjunct in a regimen of weight reduction based on exercise, behavioral modification and caloric restriction in the management of exogenous obesity, and that co-administration of phentermine with other drugs for weight loss is not recommended [see INDICATIONS AND USAGE (1) and WARNINGS ANDPRECAUTIONS (5.1)].

Patients must be instructed on how much phentermine to take, and when and how to take it [see DOSAGE AND ADMINISTRATION (3)].

Advise pregnant women and nursing mothers not to use phentermine [see USE IN SPECIFIC POPULATIONS (8.1, 8.3)].

Patients must be informed about the risks of use of phentermine (including the risks discussed in Warnings and Precautions), about the symptoms of potential adverse reactions and when to contact a physician and/or take other action. The risks include, but are not limited to:

• Development of primary pulmonary hypertension [see WARNINGS AND PRECAUTIONS (5.2)]

• Development of serious valvular heart disease [see WARNINGS AND PRECAUTIONS (5.3)]

• Effects on the ability to engage in potentially hazardous tasks [see WARNINGS AND PRECAUTIONS (5.5)]

• The risk of an increase in blood pressure [see WARNINGS AND PRECAUTIONS (5.8) and ADVERSE REACTIONS (6)]

• The risk of interactions [see CONTRAINDICATIONS (4), WARNINGS AND PRECAUTIONS (5.7, 5.9) and DRUG INTERACTIONS (7)]

See also, for example, ADVERSE REACTIONS (6) and USE IN SPECIFIC POPULATIONS (8).
The patients must also be informed about
• the potential for developing tolerance and actions if they suspect development of tolerance [see WARNINGS AND PRECAUTIONS (5.4)] and
• the risk of dependence and the potential consequences of abuse [see WARNINGS AND PRECAUTIONS (5.6), DRUG ABUSE AND DEPENDENCE (9), and OVERDOSAGE (10)].

Tell patients to keep phentermine in a safe place to prevent theft, accidental overdose, misuse or abuse. Selling or giving away phentermine may harm others and is against the law.

Rx Only

Manufactured & Distributed By:
Sunrise Pharmaceutical, Inc.
Rahway, New Jersey 07065

Revised: 09/2024
5362/01

PACKAGE LABEL

Phentermine Hydrochloride 30mg (CIV) Capsules